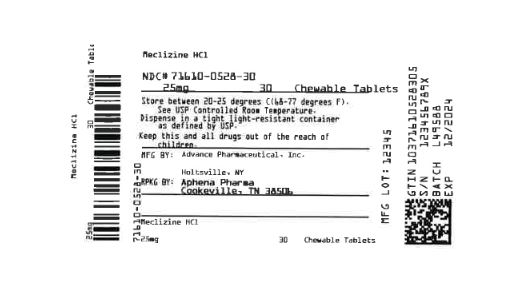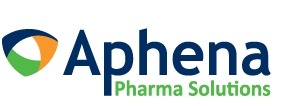 DRUG LABEL: Meclizine HCL
NDC: 71610-528 | Form: TABLET, CHEWABLE
Manufacturer: Aphena Pharma Solutions - Tennessee, LLC
Category: otc | Type: HUMAN OTC DRUG LABEL
Date: 20250109

ACTIVE INGREDIENTS: MECLIZINE HYDROCHLORIDE 25 mg/1 1
INACTIVE INGREDIENTS: ASPARTAME; CROSCARMELLOSE SODIUM; DEXTROSE; FD&C RED NO. 40; RASPBERRY; MAGNESIUM STEARATE; MICROCRYSTALLINE CELLULOSE; SUCROSE

Motion Sickness

Active ingredient

Meclizine Hydrochloride 25 mg

Purpose

Antiemetic

Uses

For the prevention and treatment of nausea, vomiting or dizziness associated with motion sickness. For other uses consult your doctor

Warnings

Ask a doctor before use if you have

- glaucoma
- a breathing problem such as emphysema or chronic bronchitis
- trouble urinating due to an elarged prostate gland

Ask a doctor or pharmacist before use if you are taking sedatives or tranquilizers

When using this product

- you may get drowsy
- avoid alcoholic drinks
- alcohol, sedatives and tranquilizers may increse drowsiness
- be careful when driving a moor vehicle or operating machinery

Directions

take dose one hour before travel starts
tablets can be chewed or swallowed whole with water

adults & children 12 years and over:

- take 1-2 tablets once daily

children under 12 years:

- ask a doctor

Keep out of reach of children.

In case of overdose, get medical help or contact a Poison Control Center right away.

OTHER INFORMATION

Phenylketonurics:
each tablet contains:
phenylalanine 0.28 mg
store at room temparature 15 - 30 °C

Questions or Comments

Call 804-270-4498, 8.30 am-4.30 pm ET, Monday - Friday
TAMPER EVIDENT: DO NOT USE IF IMPRINTED SAFETY SEAL UNDER CAP IS BROKEN OR MISSING

Inactive ingredients

Aspartame, compressible sugar, croscarmellose sodium, dextrose, FD&C red 40 (al-lake), magnesium stearate, microcrystalline cellulose, raspberry flavor

Repackaging Information

Please reference the How Suppliedsection listed above for a description of individual tablets. This drug product has been received by Aphena Pharma - TN in a manufacturer or distributor packaged configuration and repackaged in full compliance with all applicable cGMP regulations. The package configurations available from Aphena are listed below:

Count | 25 mg
30 | 71610-0528-30
90 | 71610-0528-60

Store between 20°-25°C (68°-77°F). See USP Controlled Room Temperature. Dispense in a tight light-resistant container as defined by USP. Keep this and all drugs out of the reach of children.

Repackaged by:
Cookeville, TN 38506
20210415JH

PRINCIPAL DISPLAY PANEL - 25 mg

NDC 71610-528 - Meclizine HCl 25 mg Chewable Tablets